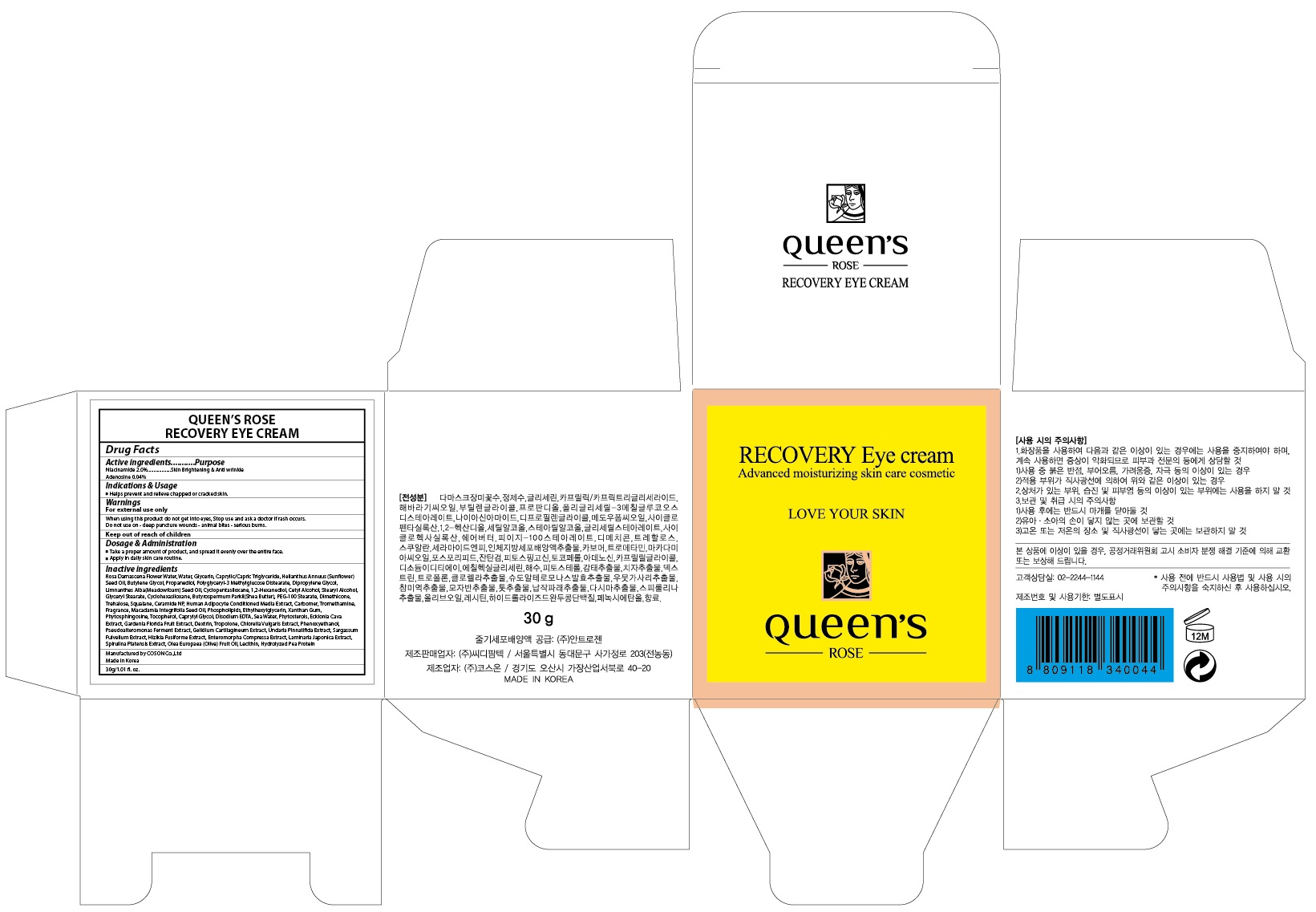 DRUG LABEL: QUEENS ROSE RECOVERY EYE
NDC: 71252-040 | Form: CREAM
Manufacturer: Cdpharmtec Co.,ltd
Category: otc | Type: HUMAN OTC DRUG LABEL
Date: 20170324

ACTIVE INGREDIENTS: Niacinamide 0.6 g/30 mL; Adenosine 0.012 g/30 mL
INACTIVE INGREDIENTS: ROSA DAMASCENA FLOWER OIL; Water

ACTIVE INGREDIENT

Active ingredients: Niacinamide 2.0%, Adenosine 0.04%

INACTIVE INGREDIENT

Inactive ingredients: Rosa Damascena Flower Water, Water, Glycerin, Caprylic/Capric Triglyceride, Helianthus Annuus (Sunflower) Seed Oil, Butylene Glycol, Propanediol, Polyglyceryl-3 Methylglucose Distearate, Dipropylene Glycol, Limnanthes Alba(Meadowfoam) Seed Oil, Cyclopentasiloxane, 1,2-Hexanediol, Cetyl Alcohol, Stearyl Alcohol, Glyceryl Stearate, Cyclohexasiloxane, Butyrospermum Parkii(Shea Butter), PEG-100 Stearate, Dimethicone, Trehalose, Squalane, Ceramide NP, Human Adipocyte Conditioned Media Extract, Carbomer, Tromethamine, Fragrance, Macadamia Integrifolia Seed Oil, Phospholipids, Ethylhexylglycerin, Xanthan Gum, Phytosphingosine, Tocopherol, Caprylyl Glycol, Disodium EDTA, Sea Water, Phytosterols, Ecklonia Cava Extract, Gardenia Florida Fruit Extract, Dextrin, Tropolone, Chlorella Vulgaris Extract, Phenoxyethanol, Pseudoalteromonas Ferment Extract, Gelidium Cartilagineum Extract, Undaria Pinnatifida Extract, Sargassum Fulvellum Extract, Hizikia Fusiforme Extract, Enteromorpha Compressa Extract, Laminaria Japonica Extract, Spirulina Platensis Extract, Olea Europaea (Olive) Fruit Oil, Lecithin, Hydrolyzed Pea Protein

PURPOSE

Purpose: Skin Brightening & Anti wrinkle

WARNINGS

Warnings: For external use only When using this product do not get into eyes, Stop use and ask a doctor if rash occurs. Do not use on - deep puncture wounds - animal bites - serious burns.

KEEP OUT OF REACH OF CHILDREN

INDICATIONS & USAGE

Indications & Usage: Helps prevent and relieve chapped or cracked skin.

DOSAGE & ADMINISTRATION

Dosage & Administration: - Take a proper amount of product, and spread it evenly over the entire face. - Apply in daily skin care routine.